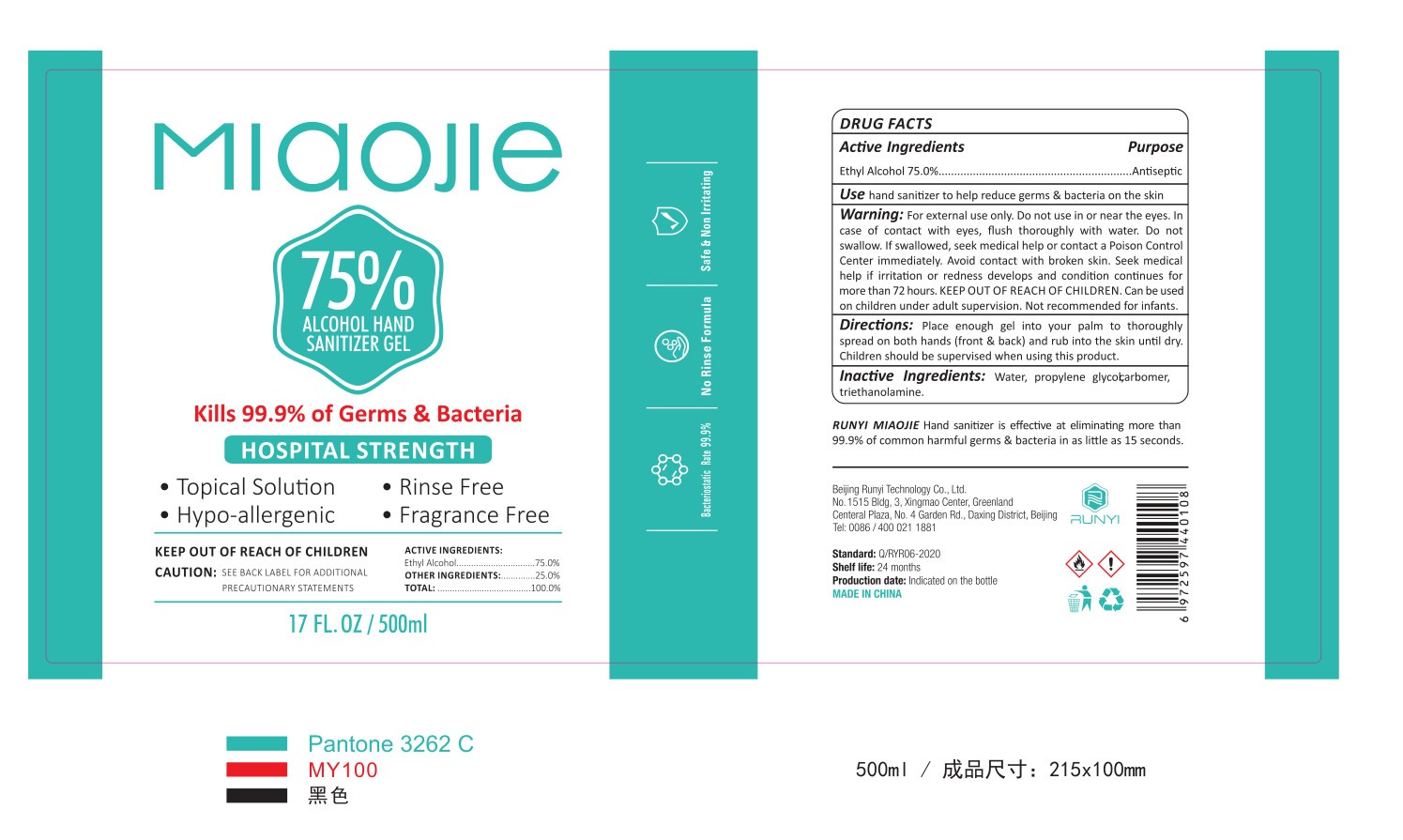 DRUG LABEL: RUNYI MIAOJIE Hand sanitizer
NDC: 95697-001 | Form: GEL
Manufacturer: Paper Plus Connection, Inc.
Category: otc | Type: HUMAN OTC DRUG LABEL
Date: 20200729

ACTIVE INGREDIENTS: ALCOHOL 375 mL/500 mL
INACTIVE INGREDIENTS: WATER; CARBOMER HOMOPOLYMER, UNSPECIFIED TYPE; TROLAMINE; PROPYLENE GLYCOL

DOSAGE AND ADMINISTRATION

Store in a cool and dry place

INACTIVE INGREDIENT

Water,carbomer, triethanolamine,propylene glycol

INDICATIONS AND USAGE

Place enough gel into your palm to thoroughly .spread on both hands (front & back) and rub into the skin until dry.

ACTIVE INGREDIENT

ethanol

keep out of reach of children

PURPOSE

Disinfection
Sterilization
No Rinseing

WARNINGS

For external use only. Do not use in or near the eyes. In case of contact with eyes, flush thoroughly with water. Do not swallow. If swallowed, seek medical help or contact a Poison Control Center immediately. Avoid contact with broken skin. Seek medical help if irritation or redness develops and condition continues for more than 72 hours. KEEP OUT OF REACH OF CHILDREN. Can be used
on children under adult supervision. Not recommended for infants.